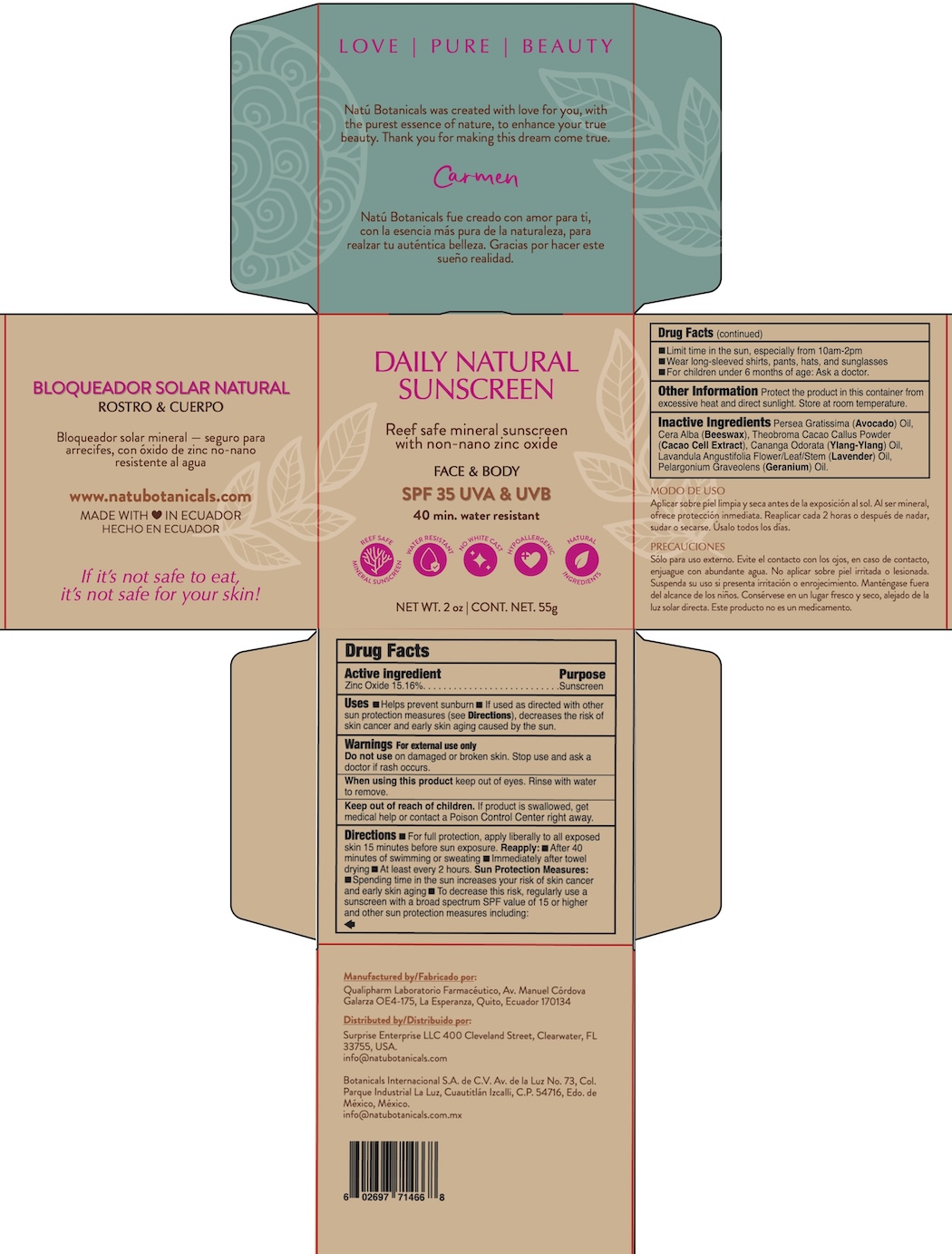 DRUG LABEL: Natu Botanicals DAILY NATURAL SUNSCREEN SPF 35
NDC: 85860-100 | Form: CREAM
Manufacturer: Surprise Enterprise LLC
Category: otc | Type: HUMAN OTC DRUG LABEL
Date: 20250630

ACTIVE INGREDIENTS: ZINC OXIDE 15.16 g/100 g
INACTIVE INGREDIENTS: THEOBROMA CACAO (COCOA) SEED POWDER; PELARGONIUM GRAVEOLENS FLOWER OIL; LAVENDER OIL; YELLOW WAX; YLANG-YLANG OIL; AVOCADO OIL

Natu DAILY NATURAL SUNSCREEN SPF 35

Drug Facts

Active Ingredient

Zinc Oxide 15.16%

Purpose

Sunscreen

Uses

- Helps prevent sunburn
- If used as directed with other sun protection measures (see Directions), decreases the risk of skin cancer and early skin aging caused by the sun.

Warnings

For external use only

DO NOT USE

Do not useon damaged or broken skin. Stop and ask a doctor if rash occurs.

WHEN USING

When using this productkeep out of eyes. Rinse with water to remove.

Keep out of reach of children.If product is swallowed, get medical help or contact a Poison Control Center right away.

Directions

- For full protection, apply liberally to all exposed skin 15 minutes before sun exposure.

Reapply:

- After 40 minutes of swimming or sweating
- Immediately after towel drying
- At least every 2 hours

Sun Protection Measures:

- Spending time in the sun increases your risk of skin cancer and early skin aging
- To decrease this risk, regularly use a sunscreen with a broad spectrum SPF value of 15 or higher and other sun protection measures including:
  - Limit time in the sun, especially from 10am-2pm
  - Wear long-sleeved shirts, pants, hats, and sunglasses
- For children under 6 months of age: ask a doctor.

Other Information

Other Information Protect the product in this container from excessive heat and direct sunlight. Store at room temperature.

Inactive ingredients

Persea Gratissima (Avocado) Oil, Cera Alba (Beeswax), Theobroma Cacao Callus Powder (Cacao Cell Extract), Cananga Odorata (Ylang-Ylang) Oil, Lavandula Angustifolia Flower/Leaf/Stem (Lavender) Oil, Pelargonium Graveolens (Geranium) Oil